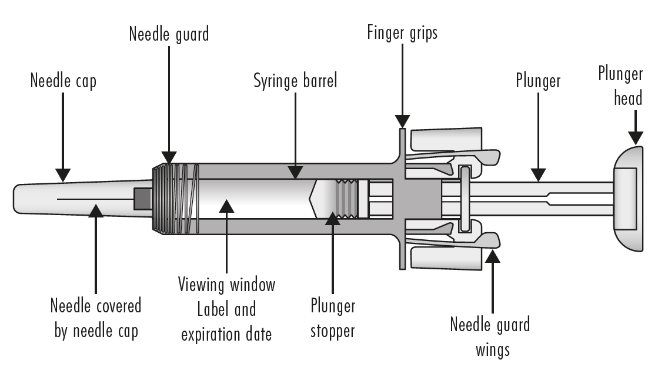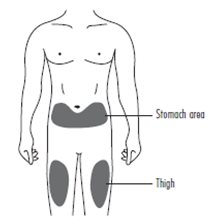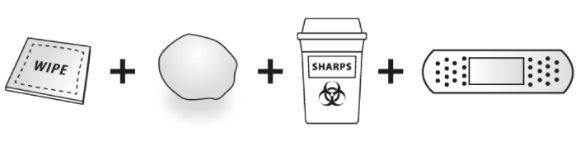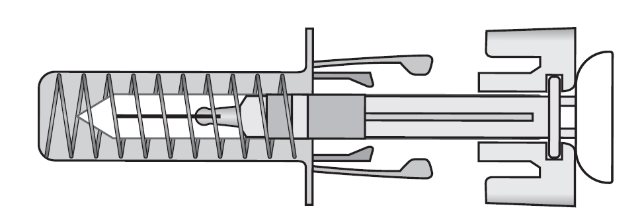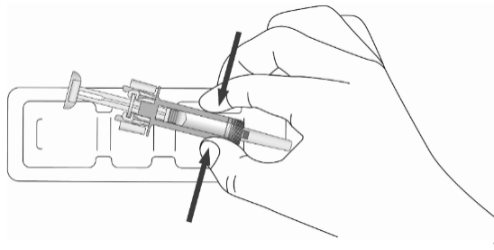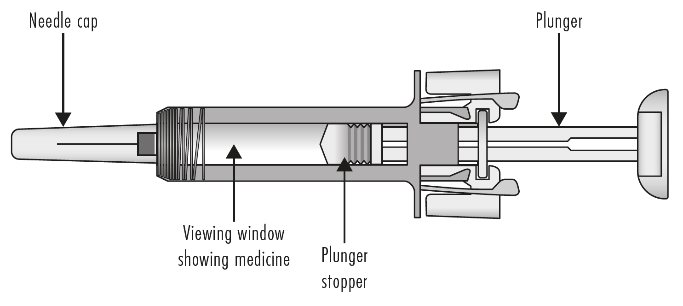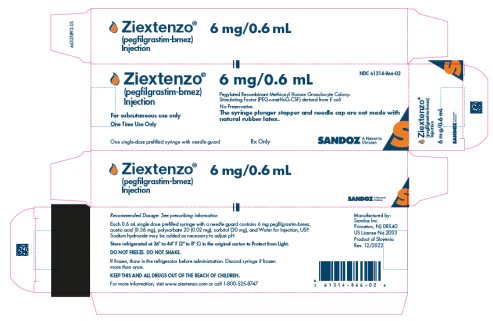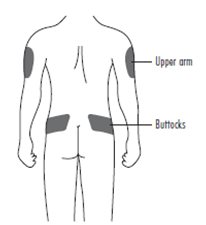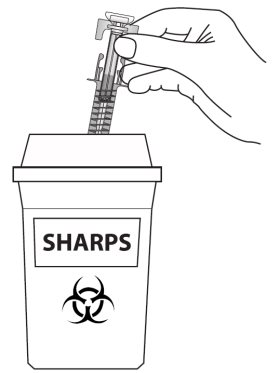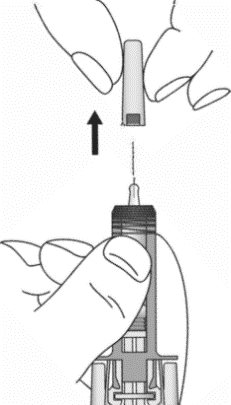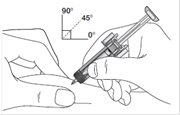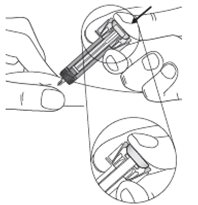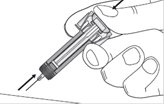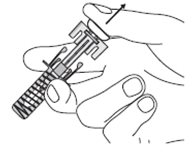 DRUG LABEL: ZIEXTENZO
NDC: 61314-866 | Form: INJECTION
Manufacturer: Sandoz Inc
Category: prescription | Type: HUMAN PRESCRIPTION DRUG LABEL
Date: 20240227

ACTIVE INGREDIENTS: PEGFILGRASTIM 6 mg/0.6 mL
INACTIVE INGREDIENTS: ACETIC ACID 0.36 mg/0.6 mL; POLYSORBATE 20 0.02 mg/0.6 mL; SORBITOL 30 mg/0.6 mL; SODIUM HYDROXIDE; WATER

HIGHLIGHTS OF PRESCRIBING INFORMATION

These highlights do not include all the information needed to use ZIEXTENZO safely and effectively. See full prescribing information for ZIEXTENZO.
ZIEXTENZO® (pegfilgrastim-bmez) injection, for subcutaneous use
Initial U.S. Approval: 2019
ZIEXTENZO (pegfilgrastim-bmez) is biosimilar* to NEULASTA® (pegfilgrastim).

RECENT MAJOR CHANGES

Indications and Usage, Patients with Hematopoietic Subsyndrome of Acute

Radiation Syndrome (1.2) 02/2024

Dosage and Administration, Patients with Hematopoietic Subsyndrome of

Acute Radiation Syndrome (2.2) 02/2024

1 INDICATIONS AND USAGE

ZIEXTENZO is a leukocyte growth factor indicated to

- Decrease the incidence of infection, as manifested by febrile neutropenia, in patients with non-myeloid malignancies receiving myelosuppressive anti-cancer drugs associated with a clinically significant incidence of febrile neutropenia. (1.1)
- Increase survival in patients acutely exposed to myelosuppressive doses of radiation (Hematopoietic Subsyndrome of Acute Radiation Syndrome). (1.2)

Limitations of Use

ZIEXTENZO is not indicated for the mobilization of peripheral blood progenitor cells for hematopoietic stem cell transplantation.

2 DOSAGE AND ADMINISTRATION

Patients with cancer receiving myelosuppressive chemotherapy

- 6 mg administered subcutaneously once per chemotherapy cycle. (2.1)
- Do not administer between 14 days before and 24 hours after administration of cytotoxic chemotherapy. (2.1)
- Use weight based dosing for pediatric patients weighing less than 45 kg; refer to Table 1. (2.3)

Patients acutely exposed to myelosuppressive doses of radiation

- Two doses, 6 mg each, administered subcutaneously one week apart. Administer the first dose as soon as possible after suspected or confirmed exposure to myelosuppressive doses of radiation, and a second dose one week after. (2.2)
- Use weight based dosing for pediatric patients weighing less than 45 kg; refer to Table 1. (2.3)

3 DOSAGE FORMS AND STRENGTHS

Injection: 6 mg/0.6 mL solution in a single-dose prefilled syringe for manual use only. (3)

4 CONTRAINDICATIONS

Patients with a history of serious allergic reactions to human granulocyte colony-stimulating factors such as pegfilgrastim products or filgrastim products. (4)

5 WARNINGS AND PRECAUTIONS

- Fatal splenic rupture: Evaluate patients who report left upper abdominal or shoulder pain for an enlarged spleen or splenic rupture. (5.1)
- Acute respiratory distress syndrome (ARDS): Evaluate patients who develop fever, lung infiltrates, or respiratory distress. Discontinue ZIEXTENZO in patients with ARDS. (5.2)
- Serious allergic reactions, including anaphylaxis: Permanently discontinue ZIEXTENZO in patients with serious allergic reactions. (5.3)
- Fatal sickle cell crises: Discontinue ZIEXTENZO if sickle cell crisis occurs. (5.4)
- Glomerulonephritis: Evaluate and consider dose-reduction or interruption of ZIEXTENZO if causality is likely. (5.5)
- Thrombocytopenia: Monitor platelet counts. (5.7)
- Myelodysplastic Syndrome (MDS) and Acute Myeloid Leukemia (AML): Monitor patients with breast and lung cancer using ZIEXTENZO in conjunction with chemotherapy and/or radiotherapy for signs and symptoms of MDS/AML. (5.10)

6 ADVERSE REACTIONS

Most common adverse reactions (≥ 5% difference in incidence compared to placebo) are bone pain and pain in extremity. (6.1)

*Biosimilar means that the biological product is approved based on data demonstrating that it is highly similar to an FDA-approved biological product, known as a reference product, and that there are no clinically meaningful differences between the biosimilar product and the reference product. Biosimilarity of ZIEXTENZO has been demonstrated for the condition(s) of use (e.g., indication(s), dosing regimen(s)), strength(s), dosage form(s), and route(s) of administration described in its Full Prescribing Information.

To report SUSPECTED ADVERSE REACTIONS, contact Sandoz Inc. at 1-800-525-8747 or FDA at 1-800-FDA-1088 or www.fda.gov/medwatch.

FULL PRESCRIBING INFORMATION

1 INDICATIONS AND USAGE

1.1 Patients with Cancer Receiving Myelosuppressive Chemotherapy

ZIEXTENZO is indicated to decrease the incidence of infection, as manifested by febrile neutropenia, in patients with non-myeloid malignancies receiving myelosuppressive anti-cancer drugs associated with a clinically significant incidence of febrile neutropenia [see Clinical Studies (14.1)].

Limitations of Use

ZIEXTENZO is not indicated for the mobilization of peripheral blood progenitor cells for hematopoietic stem cell transplantation.

1.2 Patients with Hematopoietic Subsyndrome of Acute Radiation Syndrome

ZIEXTENZO is indicated to increase survival in patients acutely exposed to myelosuppressive doses of radiation [see Dosage and Administration (2.2) and Clinical Studies (14.2)].

2 DOSAGE AND ADMINISTRATION

2.1 Patients with Cancer Receiving Myelosuppressive Chemotherapy

The recommended dosage of ZIEXTENZO is a single subcutaneous injection of 6 mg administered once per chemotherapy cycle. For dosing in pediatric patients weighing less than 45 kg, refer to Table 1. Do not administer ZIEXTENZO between 14 days before and 24 hours after administration of cytotoxic chemotherapy.

2.2 Patients with Hematopoietic Subsyndrome of Acute Radiation Syndrome

The recommended dose of ZIEXTENZO is two doses, 6 mg each, administered subcutaneously one week apart. For dosing in pediatric patients weighing less than 45 kg, refer to Table 1. Administer the first dose as soon as possible after suspected or confirmed exposure to radiation levels greater than 2 gray (Gy). Administer the second dose one week after the first dose.

Obtain a baseline complete blood count (CBC). Do not delay administration of ZIEXTENZO if a CBC is not readily available. Estimate a patient’s absorbed radiation dose (i.e., level of radiation exposure) based on information from public health authorities, biodosimetry if available, or clinical findings such as time to onset of vomiting or lymphocyte depletion kinetics.

2.3 Administration

ZIEXTENZO is administered subcutaneously via a single-dose prefilled syringe for manual use.

Prior to use‚ remove the carton from the refrigerator and allow the ZIEXTENZO prefilled syringe to reach room temperature for a minimum of 15-30 minutes. Discard any prefilled syringe left at room temperature for greater than 120 hours.

Parenteral drug products should be inspected visually for particulate matter and discoloration prior to administration, whenever solution and container permit. ZIEXTENZO is supplied as a clear and colorless to slightly yellowish solution. Do not administer ZIEXTENZO if discoloration or particulates are observed.

The ZIEXTENZO syringe plunger stopper and needle cap are not made with natural rubber latex.

Pediatric Patients weighing less than 45 kg

The ZIEXTENZO prefilled syringe is not designed to allow for direct administration of doses less than 0.6 mL (6 mg). The syringe does not bear graduation marks, which are necessary to accurately measure doses of ZIEXTENZO less than 0.6 mL (6 mg) for direct administration to patients. Thus, the direct administration to patients requiring dosing of less than 0.6 mL (6 mg) is not recommended due to the potential for dosing errors. Refer to Table 1.

Table 1. Dosing of ZIEXTENZO for pediatric patients weighing less than 45 kg
Body Weight | ZIEXTENZO Dose | Volume to Administer
Less than 10 kg [For pediatric patients weighing less than 10 kg, administer 0.1 mg/kg (0.01 mL/kg) of ZIEXTENZO.] | See below | See below
10 - 20 kg | 1.5 mg | 0.15 mL
21 - 30 kg | 2.5 mg | 0.25 mL
31 - 44 kg | 4 mg | 0.4 mL

3 DOSAGE FORMS AND STRENGTHS

ZIEXTENZO is a clear, colorless to slightly yellowish, preservative-free solution available as:

- Injection: 6 mg/0.6 mL in a single-dose prefilled syringe for manual use only.

4 CONTRAINDICATIONS

ZIEXTENZO is contraindicated in patients with a history of serious allergic reactions to pegfilgrastim products or filgrastim products. Reactions have included anaphylaxis [see Warnings and Precautions (5.3)].

5 WARNINGS AND PRECAUTIONS

5.1 Splenic Rupture

Splenic rupture, including fatal cases, can occur following the administration of pegfilgrastim products. Evaluate for an enlarged spleen or splenic rupture in patients who report left upper abdominal or shoulder pain after receiving ZIEXTENZO.

5.2 Acute Respiratory Distress Syndrome

Acute respiratory distress syndrome (ARDS) can occur in patients receiving pegfilgrastim products. Evaluate patients who develop fever and lung infiltrates or respiratory distress after receiving ZIEXTENZO, for ARDS. Discontinue ZIEXTENZO in patients with ARDS.

5.3 Serious Allergic Reactions

Serious allergic reactions, including anaphylaxis, can occur in patients receiving pegfilgrastim products. The majority of reported events occurred upon initial exposure. Allergic reactions, including anaphylaxis, can recur within days after the discontinuation of initial anti-allergic treatment. Permanently discontinue ZIEXTENZO in patients with serious allergic reactions. Do not administer ZIEXTENZO to patients with a history of serious allergic reactions to pegfilgrastim products or filgrastim products.

5.4 Use in Patients with Sickle Cell Disorders

Severe and sometimes fatal sickle cell crises can occur in patients with sickle cell disorders receiving pegfilgrastim products. Discontinue ZIEXTENZO if sickle cell crisis occurs.

5.5 Glomerulonephritis

Glomerulonephritis has occurred in patients receiving pegfilgrastim products. The diagnoses were based upon azotemia, hematuria (microscopic and macroscopic), proteinuria, and renal biopsy. Generally, events of glomerulonephritis resolved after dose-reduction or discontinuation of pegfilgrastim products. If glomerulonephritis is suspected, evaluate for cause. If causality is likely, consider dose-reduction or interruption of ZIEXTENZO.

5.6 Leukocytosis

White blood cell (WBC) counts of 100 x 10^9/L or greater have been observed in patients receiving pegfilgrastim products. Monitoring of complete blood count (CBC) during ZIEXTENZO therapy is recommended.

5.7 Thrombocytopenia

Thrombocytopenia has been reported in patients receiving pegfilgrastim products. Monitor platelet counts.

5.8 Capillary Leak Syndrome

Capillary leak syndrome has been reported after G-CSF administration, including pegfilgrastim products, and is characterized by hypotension, hypoalbuminemia, edema and hemoconcentration. Episodes vary in frequency, severity and may be life-threatening if treatment is delayed. Patients who develop symptoms of capillary leak syndrome should be closely monitored and receive standard symptomatic treatment, which may include a need for intensive care.

5.9 Potential for Tumor Growth Stimulatory Effects on Malignant Cells

The granulocyte colony-stimulating factor (G-CSF) receptor through which pegfilgrastim products and filgrastim products act has been found on tumor cell lines. The possibility that pegfilgrastim products act as a growth factor for any tumor type, including myeloid malignancies and myelodysplasia, diseases for which pegfilgrastim products are not approved, cannot be excluded.

5.10 Myelodysplastic Syndrome (MDS) and Acute Myeloid Leukemia (AML) in Patients with Breast and Lung Cancer

MDS and AML have been associated with the use of pegfilgrastim products in conjunction with chemotherapy and/or radiotherapy in patients with breast and lung cancer. Monitor patients for signs and symptoms of MDS/AML in these settings.

5.11 Aortitis

Aortitis has been reported in patients receiving pegfilgrastim products. It may occur as early as the first week after start of therapy. Manifestations may include generalized signs and symptoms such as fever, abdominal pain, malaise, back pain, and increased inflammatory markers (e.g., c-reactive protein and white blood cell count). Consider aortitis in patients who develop these signs and symptoms without known etiology. Discontinue ZIEXTENZO if aortitis is suspected.

5.12 Nuclear Imaging

Increased hematopoietic activity of the bone marrow in response to growth factor therapy has been associated with transient positive bone imaging changes. This should be considered when interpreting bone imaging results.

6 ADVERSE REACTIONS

The following clinically significant adverse reactions are discussed in greater detail in other sections of the labeling:

- Splenic Rupture [see Warnings and Precautions (5.1)]
- Acute Respiratory Distress Syndrome [see Warnings and Precautions (5.2)]
- Serious Allergic Reactions [see Warnings and Precautions (5.3)]
- Use in Patients with Sickle Cell Disorders [see Warnings and Precautions (5.4)]
- Glomerulonephritis [see Warnings and Precautions (5.5)]
- Leukocytosis [see Warnings and Precautions (5.6)]
- Thrombocytopenia [see Warnings and Precautions (5.7)]
- Capillary Leak Syndrome [see Warnings and Precautions (5.8)]
- Potential for Tumor Growth Stimulatory Effects on Malignant Cells [see Warnings and Precautions (5.9)]
- Myelodysplastic syndrome [see Warnings and Precautions (5.10)]
- Acute myeloid leukemia [see Warnings and Precautions (5.10)]
- Aortitis [see Warnings and Precautions (5.11)]

6.1 Clinical Trials Experience

Because clinical trials are conducted under widely varying conditions, adverse reaction rates observed in the clinical trials of a drug cannot be directly compared with rates in the clinical trials of another drug and may not reflect the rates observed in clinical practice.

Pegfilgrastim clinical trials safety data are based upon 932 patients receiving pegfilgrastim in seven randomized clinical trials. The population was 21 to 88 years of age and 92% female. The ethnicity was 75% Caucasian, 18% Hispanic, 5% Black, and 1% Asian. Patients with breast (n = 823), lung and thoracic tumors (n = 53) and lymphoma (n = 56) received pegfilgrastim after nonmyeloablative cytotoxic chemotherapy. Most patients received a single 100 mcg/kg (n = 259) or a single 6 mg (n = 546) dose per chemotherapy cycle over 4 cycles.

The following adverse reaction data in Table 2 are from a randomized, double-blind, placebo-controlled study in patients with metastatic or non-metastatic breast cancer receiving docetaxel 100 mg/m^2 every 21 days (Study 3). A total of 928 patients were randomized to receive either 6 mg pegfilgrastim (n = 467) or placebo (n = 461). The patients were 21 to 88 years of age and 99% female. The ethnicity was 66% Caucasian, 31% Hispanic, 2% Black, and < 1% Asian, Native American, or other.

The most common adverse reactions occurring in ≥ 5% of patients and with a between-group difference of ≥ 5% higher in the pegfilgrastim arm in placebo-controlled clinical trials are bone pain and pain in extremity.

Table 2. Adverse Reactions with ≥ 5% Higher Incidence in Pegfilgrastim Patients Compared to Placebo in Study 3
Body System Adverse Reaction | Placebo (N = 461) | Pegfilgrastim 6 mg SC on Day 2 (N = 467)
Musculoskeletal and connective tissue disorders
Bone pain | 26% | 31%
Pain in extremity | 4% | 9%

Leukocytosis

In clinical studies, leukocytosis (WBC counts > 100 x 10^9 /L) was observed in less than 1% of 932 patients with non-myeloid malignancies receiving pegfilgrastim. No complications attributable to leukocytosis were reported in clinical studies.

6.2 Immunogenicity

The observed incidence of anti-drug antibodies is highly dependent on the sensitivity and specificity of the assay. Differences in assay methods preclude meaningful comparisons of the incidence of anti-drug antibodies in the studies described below with the incidence of anti-drug antibodies in other studies, including those of pegfilgrastim or of other pegfilgrastim products.

Binding antibodies to pegfilgrastim were detected using a BIAcore assay. The approximate limit of detection for this assay is 500 ng/mL. Pre-existing binding antibodies were detected in approximately 6% (51/849) of patients with metastatic breast cancer. Four of 521 pegfilgrastim-treated subjects who were negative at baseline developed binding antibodies to pegfilgrastim following treatment. None of these 4 patients had evidence of neutralizing antibodies detected using a cell-based bioassay.

6.3 Postmarketing Experience

The following adverse reactions have been identified during post approval use of pegfilgrastim products. Because these reactions are reported voluntarily from a population of uncertain size, it is not always possible to reliably estimate their frequency or establish a causal relationship to drug exposure.

- Splenic rupture and splenomegaly (enlarged spleen) [see Warnings and Precautions (5.1)]
- Acute respiratory distress syndrome (ARDS) [see Warnings and Precautions (5.2)]
- Allergic reactions/hypersensitivity, including anaphylaxis, skin rash, urticaria, generalized erythema, and flushing [see Warnings and Precautions (5.3)]
- Sickle cell crisis [see Warnings and Precautions (5.4)]
- Glomerulonephritis [see Warnings and Precautions (5.5)]
- Leukocytosis [see Warnings and Precautions (5.6)]
- Thrombocytopenia [see Warnings and Precautions (5.7)]
- Capillary Leak Syndrome [see Warnings and Precautions (5.8)]
- Injection site reactions
- Sweet’s syndrome (acute febrile neutrophilic dermatosis), cutaneous vasculitis
- Myelodysplastic syndrome (MDS) and acute myeloid leukemia (AML) in patients with breast and lung cancer receiving chemotherapy and/or radiotherapy [see Warnings and Precautions (5.10)]
- Aortitis [see Warnings and Precautions (5.11)]
- Alveolar hemorrhage

8 USE IN SPECIFIC POPULATIONS

8.1 Pregnancy

Risk Summary

Although available data with ZIEXTENZO or pegfilgrastim product use in pregnant women are insufficient to establish whether there is a drug associated risk of major birth defects, miscarriage, or adverse maternal or fetal outcomes, there are available data from published studies in pregnant women exposed to filgrastim products. These studies have not established an association of filgrastim product use during pregnancy with major birth defects, miscarriage, or adverse maternal or fetal outcomes.

In animal studies, no evidence of reproductive/developmental toxicity occurred in the offspring of pregnant rats that received cumulative doses of pegfilgrastim approximately 10 times the recommended human dose (based on body surface area). In pregnant rabbits, increased embryolethality and spontaneous abortions occurred at 4 times the maximum recommended human dose simultaneously with signs of maternal toxicity (see Data).

The estimated background risk of major birth defects and miscarriage for the indicated population is unknown. All pregnancies have a background risk of birth defect, loss, or other adverse outcomes. In the U.S. general population, the estimated background risks of major birth defects and miscarriage in clinically recognized pregnancies is 2-4% and 15-20%, respectively.

Data

Animal Data

Pregnant rabbits were dosed with pegfilgrastim subcutaneously every other day during the period of organogenesis. At cumulative doses ranging from the approximate human dose to approximately 4 times the recommended human dose (based on body surface area), the treated rabbits exhibited decreased maternal food consumption, maternal weight loss, as well as reduced fetal body weights and delayed ossification of the fetal skull; however, no structural anomalies were observed in the offspring from either study. Increased incidences of post-implantation losses and spontaneous abortions (more than half the pregnancies) were observed at cumulative doses approximately 4 times the recommended human dose, which were not seen when pregnant rabbits were exposed to the recommended human dose.

Three studies were conducted in pregnant rats dosed with pegfilgrastim at cumulative doses up to approximately 10 times the recommended human dose at the following stages of gestation: during the period of organogenesis, from mating through the first half of pregnancy, and from the first trimester through delivery and lactation. No evidence of fetal loss or structural malformations was observed in any study. Cumulative doses equivalent to approximately 3 and 10 times the recommended human dose resulted in transient evidence of wavy ribs in fetuses of treated mothers (detected at the end of gestation but no longer present in pups evaluated at the end of lactation).

8.2 Lactation

Risk Summary

There are no data on the presence of pegfilgrastim products in human milk, the effects on the breastfed child, or the effects on milk production. Other filgrastim products are secreted poorly into breast milk, and filgrastim products are not absorbed orally by neonates. The developmental and health benefits of breastfeeding should be considered along with the mother’s clinical need for ZIEXTENZO and any potential adverse effects on the breastfed child from ZIEXTENZO or from the underlying maternal condition.

8.4 Pediatric Use

The safety and effectiveness of ZIEXTENZO have been established in pediatric patients. No overall differences in safety were identified between adult and pediatric patients based on postmarketing surveillance and review of the scientific literature.

Use of ZIEXTENZO in pediatric patients for chemotherapy-induced neutropenia is based on ZIEXTENZO’s approval as a biosimilar to pegfilgrastim and evidence from adequate and well-controlled studies of pegfilgrastim in adults with additional pharmacokinetic and safety data of pegfilgrastim in pediatric patients with sarcoma [see Clinical Pharmacology (12.3) and Clinical Studies (14.1)].

The use of ZIEXTENZO to increase survival in pediatric patients acutely exposed to myelosuppressive doses of radiation is based on ZIEXTENZO’s approval as a biosimilar to pegfilgrastim and evidence from efficacy studies of pegfilgrastim conducted in animals and clinical data supporting the use of pegfilgrastim in patients with cancer receiving myelosuppressive chemotherapy. Efficacy studies of pegfilgrastim products could not be conducted in humans with acute radiation syndrome for ethical and feasibility reasons. Results from population modeling and simulation indicate that two doses of pegfilgrastim (Table 1), administered one week apart provide pediatric patients with exposures comparable to that in adults receiving two 6 mg doses one week apart [see Dosage and Administration (2.3), Clinical Pharmacology (12.3) and Clinical Studies (14.2)].

8.5 Geriatric Use

Of the 932 patients with cancer who received pegfilgrastim in clinical studies, 139 (15%) were aged 65 and over, and 18 (2%) were aged 75 and over. No overall differences in safety or effectiveness were observed between patients aged 65 and older and younger patients.

10 OVERDOSAGE

Overdosage of pegfilgrastim products may result in leukocytosis and bone pain. Events of edema, dyspnea, and pleural effusion have been reported in a single patient who administered pegfilgrastim on 8 consecutive days in error. In the event of overdose, the patient should be monitored for adverse reactions [see Adverse Reactions (6)].

11 DESCRIPTION

Pegfilgrastim-bmez is a covalent conjugate of recombinant methionyl human G-CSF and monomethoxypolyethylene glycol. Recombinant methionyl human G-CSF is a water-soluble 175 amino acid protein with a molecular weight of approximately 19 kilodaltons (kD). Recombinant methionyl human G-CSF is obtained from the bacterial fermentation of a strain of E coli transformed with a genetically engineered plasmid containing the human G-CSF gene. To produce pegfilgrastim-bmez, a 20 kD monomethoxypolyethylene glycol molecule is covalently bound to the N-terminal methionyl residue of recombinant methionyl human G-CSF. The average molecular weight of pegfilgrastim-bmez is approximately 39 kD.

ZIEXTENZO for manual subcutaneous injection is supplied in 0.6 mL prefilled syringes. The prefilled syringe does not bear graduation marks and is designed to deliver the entire contents of the syringe (6 mg/0.6 mL).

The delivered 0.6 mL dose from the prefilled syringe for manual subcutaneous injection contains 6 mg pegfilgrastim-bmez (based on protein weight) in a sterile, clear, colorless to slightly yellowish, preservative-free solution (pH 4.0, sodium hydroxide may be added as necessary to adjust pH) containing acetic acid (0.36 mg), polysorbate 20 (0.02 mg), sorbitol (30 mg), and Water for Injection, USP.

12 CLINICAL PHARMACOLOGY

12.1 Mechanism of Action

Pegfilgrastim products are colony-stimulating factors that act on hematopoietic cells by binding to specific cell surface receptors, thereby stimulating proliferation, differentiation, commitment, and end cell functional activation.

12.2 Pharmacodynamics

Animal data and clinical data in humans suggest a correlation between pegfilgrastim products’ exposure and the duration of severe neutropenia as a predictor of efficacy. Selection of the dosing regimen of ZIEXTENZO is based on reducing the duration of severe neutropenia.

12.3 Pharmacokinetics

The pharmacokinetics of pegfilgrastim was studied in 379 patients with cancer. The pharmacokinetics of pegfilgrastim was nonlinear, and clearance decreased with increases in dose. Neutrophil receptor binding is an important component of the clearance of pegfilgrastim, and serum clearance is directly related to the number of neutrophils. In addition to numbers of neutrophils, body weight appeared to be a factor. Patients with higher body weights experienced higher systemic exposure to pegfilgrastim after receiving a dose normalized for body weight. A large variability in the pharmacokinetics of pegfilgrastim was observed. The half-life of pegfilgrastim ranged from 15 to 80 hours after subcutaneous injection.

Specific Populations

No gender-related differences were observed in the pharmacokinetics of pegfilgrastim, and no differences were observed in the pharmacokinetics of geriatric patients (≥ 65 years of age) compared with younger patients (< 65 years of age) [see Use in Specific Populations (8.5)].

Renal Impairment

In a study of 30 subjects with varying degrees of renal dysfunction, including end stage renal disease, renal dysfunction had no effect on the pharmacokinetics of pegfilgrastim.

Pediatric Patients with Cancer Receiving Myelosuppressive Chemotherapy

The pharmacokinetics and safety of pegfilgrastim were studied in 37 pediatric patients with sarcoma in Study 4 [see Clinical Studies 14.1]. The mean (± standard deviation [SD]) systemic exposure (AUC0-inf) of pegfilgrastim after subcutaneous administration at 100 mcg/kg was 47.9 (± 22.5) mcg·hr/mL in the youngest age group (0 to 5 years, n = 11), 22.0 (± 13.1) mcg·hr/mL in the 6 to 11 years age group (n = 10), and 29.3 (± 23.2) mcg·hr/mL in the 12 to 21 years age group (n = 13). The terminal elimination half-lives of the corresponding age groups were 30.1 (± 38.2) hours, 20.2 (± 11.3) hours, and 21.2 (± 16.0) hours, respectively.

Patients Acutely Exposed to Myelosuppressive Doses of Radiation

The pharmacokinetics of pegfilgrastim products is not available in patients acutely exposed to myelosuppressive doses of radiation. Based on limited pharmacokinetic data in irradiated non-human primates, the area under the concentration-time curve (AUC), reflecting the exposure to pegfilgrastim in non-human primates following a 300 mcg/kg dose of pegfilgrastim, appears to be greater than in humans receiving a 6 mg dose. Results from population modeling and simulation indicate that two 6 mg doses of pegfilgrastim administered one week apart in adults result in clinically relevant effects on duration of grade 3 and 4 neutropenia. In addition, weight based dosing in pediatric patients weighing less than 45 kg [see Dosage and Administration, Section 2.3, Table 1] provides exposures comparable to those in adults receiving two 6 mg doses one week apart.

13 NONCLINICAL TOXICOLOGY

13.1 Carcinogenesis, Mutagenesis, Impairment of Fertility

No carcinogenicity or mutagenesis studies have been performed with pegfilgrastim products.

Pegfilgrastim did not affect reproductive performance or fertility in male or female rats at cumulative weekly doses approximately 6 to 9 times higher than the recommended human dose (based on body surface area).

14 CLINICAL STUDIES

14.1 Patients with Cancer Receiving Myelosuppressive Chemotherapy

Pegfilgrastim was evaluated in three randomized, double-blind, controlled studies. Studies 1 and 2 were active-controlled studies that employed doxorubicin 60 mg/m^2 and docetaxel 75 mg/m^2 administered every 21 days for up to 4 cycles for the treatment of metastatic breast cancer. Study 1 investigated the utility of a fixed dose of pegfilgrastim. Study 2 employed a weight-adjusted dose. In the absence of growth factor support, similar chemotherapy regimens have been reported to result in a 100% incidence of severe neutropenia (ANC < 0.5 x 10^9/L) with a mean duration of 5 to 7 days and a 30% to 40% incidence of febrile neutropenia. Based on the correlation between the duration of severe neutropenia and the incidence of febrile neutropenia found in studies with filgrastim, duration of severe neutropenia was chosen as the primary endpoint in both studies, and the efficacy of pegfilgrastim was demonstrated by establishing comparability to filgrastim-treated patients in the mean days of severe neutropenia.

In Study 1, 157 patients were randomized to receive a single subcutaneous injection of pegfilgrastim (6 mg) on day 2 of each chemotherapy cycle or daily subcutaneous filgrastim (5 mcg/kg/day) beginning on day 2 of each chemotherapy cycle. In Study 2, 310 patients were randomized to receive a single subcutaneous injection of pegfilgrastim (100 mcg/kg) on day 2 or daily subcutaneous filgrastim (5 mcg/kg/day) beginning on day 2 of each chemotherapy cycle.

Both studies met the major efficacy outcome measure of demonstrating that the mean days of severe neutropenia of pegfilgrastim-treated patients did not exceed that of filgrastim-treated patients by more than 1 day in cycle 1 of chemotherapy. The mean days of cycle 1 severe neutropenia in Study 1 were 1.8 days in the pegfilgrastim arm compared to 1.6 days in the filgrastim arm [difference in means 0.2 (95% CI -0.2, 0.6)] and in Study 2 were 1.7 days in the pegfilgrastim arm compared to 1.6 days in the filgrastim arm [difference in means 0.1 (95% CI - 0.2, 0.4)].

A secondary endpoint in both studies was days of severe neutropenia in cycles 2 through 4 with results similar to those for cycle 1.

Study 3 was a randomized, double-blind, placebo-controlled study that employed docetaxel 100 mg/m^2 administered every 21 days for up to 4 cycles for the treatment of metastatic or non-metastatic breast cancer. In this study, 928 patients were randomized to receive a single subcutaneous injection of pegfilgrastim (6 mg) or placebo on day 2 of each chemotherapy cycle. Study 3 met the major trial outcome measure of demonstrating that the incidence of febrile neutropenia (defined as temperature ≥ 38.2°C and ANC ≤ 0.5 x 10^9/L) was lower for pegfilgrastim-treated patients as compared to placebo-treated patients (1% versus 17%, respectively, p < 0.001). The incidence of hospitalizations (1% versus 14%) and IV anti-infective use (2% versus 10%) for the treatment of febrile neutropenia was also lower in the pegfilgrastim-treated patients compared to the placebo-treated patients.

Study 4 was a multicenter, randomized, open-label study to evaluate the efficacy, safety, and pharmacokinetics [see Clinical Pharmacology (12.3)] of pegfilgrastim in pediatric and young adult patients with sarcoma. Patients with sarcoma receiving chemotherapy age 0 to 21 years were eligible. Patients were randomized to receive subcutaneous pegfilgrastim as a single-dose of 100 mcg/kg (n = 37) or subcutaneous filgrastim at a dose 5 mcg/kg/day (n = 6) following myelosuppressive chemotherapy. Recovery of neutrophil counts was similar in the pegfilgrastim and filgrastim groups. The most common adverse reaction reported was bone pain.

14.2 Patients with Hematopoietic Subsyndrome of Acute Radiation Syndrome

Efficacy studies of pegfilgrastim products could not be conducted in humans with acute radiation syndrome for ethical and feasibility reasons. Approval of this indication was based on efficacy studies conducted in animals and data supporting pegfilgrastim’s effect on severe neutropenia in patients with cancer receiving myelosuppressive chemotherapy [see Dosage and Administration (2.1)].

The recommended dose of ZIEXTENZO is two doses, 6 mg each, administered one week apart for humans exposed to myelosuppressive doses of radiation. For pediatric patients weighing less than 45 kg, dosing of ZIEXTENZO is weight based and is provided in Table 1 [see Dosage and Administration (2.3)]. This dosing regimen is based on population modeling and simulation analyses. The exposure associated with this dosing regimen is expected to provide sufficient pharmacodynamic activity to treat humans exposed to myelosuppressive doses of radiation [see Clinical Pharmacology (12.3)]. The safety of pegfilgrastim at a dose of 6 mg has been assessed on the basis of clinical experience in patients with cancer receiving myelosuppressive chemotherapy.

The efficacy of pegfilgrastim for the acute radiation syndrome setting was studied in a randomized, placebo-controlled non-human primate model of radiation injury. Rhesus macaques were randomized to either a control (n = 23) or treated (n = 23) cohort. On study day 0, animals (n = 6 to 8 per irradiation day) were exposed to total body irradiation (TBI) of 7.50 ± 0.15 Gy delivered at 0.8 ± 0.03 Gy/min, representing a dose that would be lethal in 50% of animals by 60 days of follow-up (LD50/60). Animals were administered subcutaneous injections of a blinded treatment (control article [5% dextrose in water] or pegfilgrastim [300-319 mcg/kg/day]) on study day 1 and on study day 8. The primary endpoint was survival. Animals received medical management consisting of intravenous fluids, antibiotics, blood transfusions, and other support as required.

Pegfilgrastim significantly (at 0.0014 level of significance) increased 60-day survival in irradiated non-human primates: 91% survival (21/23) in the pegfilgrastim group compared to 48% survival (11/23) in the control group.

16 HOW SUPPLIED/STORAGE AND HANDLING

ZIEXTENZO single-dose prefilled syringe for manual use

ZIEXTENZO injection is a clear, colorless to slightly yellowish solution supplied in a prefilled single-dose syringe for manual use containing 6 mg pegfilgrastim-bmez, supplied with a 29-gauge, 1/2-inch needle with an UltraSafe PassiveTM Needle Guard.

The ZIEXTENZO syringe plunger stopper and needle cap are not made with natural rubber latex.

ZIEXTENZO is provided in a dispensing pack containing one sterile 6 mg/0.6 mL prefilled syringe (NDC 61314-866-02).

ZIEXTENZO prefilled syringe does not bear graduation marks and is intended only to deliver the entire contents of the syringe (6 mg/0.6 mL) for direct administration. Use of the prefilled syringe is not recommended for direct administration for pediatric patients weighing less than 45 kg who require doses that are less than the full contents of the syringe.

Store refrigerated between 36°F to 46°F (2°C to 8°C) in the carton to protect from light. Do not shake. Discard syringes stored at room temperature for more than 120 hours. Avoid freezing; if frozen, thaw in the refrigerator before administration. Discard syringe if frozen more than once.

17 PATIENT COUNSELING INFORMATION

Advise the patient to read the FDA-approved patient labeling (Patient Information and Instructions for Use).

Advise patients of the following risks and potential risks with ZIEXTENZO:

- Splenic rupture and splenomegaly
- Acute Respiratory Distress Syndrome
- Serious allergic reactions
- Sickle cell crisis
- Glomerulonephritis
- Increased risk of Myelodysplastic Syndrome and/or Acute Myeloid Leukemia in patients with breast and lung cancer who receive ZIEXTENZO in conjunction with chemotherapy and/or radiation therapy
- Capillary Leak Syndrome
- Aortitis

Advise patients acutely exposed to myelosuppressive doses of radiation (Hematopoietic Subsyndrome of Acute Radiation Syndrome) that efficacy studies of pegfilgrastim products for this indication could not be conducted in humans for ethical and feasibility reasons and that, therefore, approval of this use was based on efficacy studies conducted in animals [see Clinical Studies (14.2)].

Instruct patients who self-administer ZIEXTENZO using the single-dose prefilled syringe of the:

- Importance of following the Instructions for Use (see Instructions for Use).
- Dangers of reusing syringes.
- Importance of following local requirements for proper disposal of used syringes.

Manufactured by:

Sandoz Inc.

Princeton, NJ 08540

US License No. 2003

Patient Information

ZIEXTENZO (zee-eks-TEN-zoh)

(pegfilgrastim-bmez)

injection

Single-dose prefilled syringe

What is ZIEXTENZO?

ZIEXTENZO is a man-made form of granulocyte colony-stimulating factor (G-CSF). G-CSF is a substance produced by the body. It stimulates the growth of neutrophils, a type of white blood cell important in the body’s fight against infection.

Acute Radiation Syndrome: The effectiveness of pegfilgrastim for this use was only studied in animals, because it could not be studied in people.

Do not take ZIEXTENZO if you have had a serious allergic reaction to pegfilgrastim products or filgrastim products.

Before you receive ZIEXTENZO, tell your healthcare provider about all of your medical conditions, including if you:
2. have a sickle cell disorder.
3. have kidney problems.
4. are pregnant or plan to become pregnant. It is not known if ZIEXTENZO will harm your unborn baby.
5. are breastfeeding or plan to breastfeed. It is not known if ZIEXTENZO passes into your breast milk.

Tell your healthcare provider about all of the medicines you take, including prescription and over-the-counter medicines, vitamins, and herbal supplements.

How will I receive ZIEXTENZO?

- ZIEXTENZO is given as an injection under your skin (subcutaneous injection) by a healthcare provider. If your healthcare provider decides that the subcutaneous injections can be given at home by you or your caregiver, follow the detailed “Instructions for Use” that comes with your ZIEXTENZO for information on how to prepare and inject a dose of ZIEXTENZO.
- You and your caregiver will be shown how to prepare and inject ZIEXTENZO before you use it.
- You should not inject a dose of ZIEXTENZO to children weighing less than 45 kg from a ZIEXTENZO prefilled syringe. A dose less than 0.6 mL (6 mg) cannot be accurately measured using the ZIEXTENZO prefilled syringe.
- If you are receiving ZIEXTENZO because you are also receiving chemotherapy, the last dose of ZIEXTENZO should be injected at least 14 days before and 24 hours after your dose of chemotherapy.
- If you miss a dose of ZIEXTENZO, talk to your healthcare provider about when you should give your next dose.

What are possible side effects of ZIEXTENZO?

ZIEXTENZO may cause serious side effects, including:

- Spleen Rupture. Your spleen may become enlarged and can rupture. A ruptured spleen can cause death. Call your healthcare provider right away if you have pain in the left upper stomach area or your left shoulder.
- A serious lung problem called Acute Respiratory Distress Syndrome (ARDS). Call your healthcare provider or get emergency help right away if you have shortness of breath with or without a fever, trouble breathing, or a fast rate of breathing.
- Serious allergic reactions. ZIEXTENZO can cause serious allergic reactions. These reactions can cause a rash over your whole body, shortness of breath, wheezing, dizziness, swelling around your mouth or eyes, fast heart rate, and sweating. If you have any of these symptoms, stop using ZIEXTENZO and call your healthcare provider or get emergency medical help right away.
- Sickle cell crises. You may have a serious sickle cell crisis, which could lead to death, if you have a sickle cell disorder and receive ZIEXTENZO. Call your healthcare provider right away if you have symptoms of sickle cell crisis such as pain or difficulty breathing.
- Kidney injury (glomerulonephritis). ZIEXTENZO can cause kidney injury. Call your healthcare provider right away if you develop any of the following symptoms:
  - swelling of your face or ankles
  - blood in your urine or dark colored urine
  - you urinate less than usual
- Increased white blood cell count (leukocytosis). Your healthcare provider will check your blood during treatment with ZIEXTENZO.
- Decreased platelet count (thrombocytopenia). Your healthcare provider will check your blood during treatment with ZIEXTENZO. Tell your healthcare provider if you have unusual bleeding or bruising during treatment with ZIEXTENZO. This could be a sign of decreased platelet counts, which may reduce the ability of your blood to clot.
- Capillary Leak Syndrome. ZIEXTENZO can cause fluid to leak from blood vessels into your body’s tissues. This condition is called “Capillary Leak Syndrome” (CLS). CLS can quickly cause you to have symptoms that may become life-threatening. Get emergency medical help right away if you develop any of the following symptoms:
  - swelling or puffiness and are urinating less than usual
  - trouble breathing
  - swelling of your stomach area (abdomen) and feeling of fullness
  - dizziness or feeling faint
  - a general feeling of tiredness
- Myelodysplastic syndrome and acute myeloid leukemia. If you have breast cancer or lung cancer, when ZIEXTENZO is used with chemotherapy and radiation therapy, or with radiation therapy alone, you may have an increased risk of developing a precancerous blood condition called myelodysplastic syndrome (MDS) or a blood cancer called acute myeloid leukemia (AML). Symptoms of MDS and AML may include tiredness, fever, and easy bruising or bleeding. Call your healthcare provider if you develop these symptoms during treatment with ZIEXTENZO.
- Inflammation of the aorta (aortitis). Inflammation of the aorta (the large blood vessel which transports blood from the heart to the body) has been reported in patients who received pegfilgrastim products. Symptoms may include fever, abdominal pain, feeling tired, and back pain. Call your healthcare provider if you experience these symptoms.

The most common side effects of ZIEXTENZO are pain in the bones, arms, and legs.

These are not all the possible side effects of ZIEXTENZO.

Call your doctor for medical advice about side effects. You may report side effects to FDA at 1-800-FDA-1088.

How should I store ZIEXTENZO?

- Store ZIEXTENZO in the refrigerator between 36°F to 46°F (2°C to 8°C).
- Take ZIEXTENZO out of the refrigerator for at least 15 to 30 minutes before use and allow it to reach room temperature before preparing an injection.
- Avoid freezing. If ZIEXTENZO is accidently frozen, allow the prefilled syringe to thaw in the refrigerator before injecting.
- Do not use a ZIEXTENZO prefilled syringe that has been frozen more than 1 time. Use a new ZIEXTENZO prefilled syringe.
- Keep the prefilled syringe in the original carton to protect from light or physical damage.
- Do not shake the prefilled syringe.
- Throw away (dispose of) any ZIEXTENZO that has been left at room temperature, 68°F to 95°F (20°C to 35°C), for more than 120 hours.

Keep the ZIEXTENZO prefilled syringe out of the reach of children.

General information about the safe and effective use of ZIEXTENZO.

Medicines are sometimes prescribed for purposes other than those listed in a Patient Information leaflet. Do not use ZIEXTENZO for a condition for which it was not prescribed. Do not give ZIEXTENZO to other people, even if they have the same symptoms that you have. It may harm them. You can ask your pharmacist or healthcare provider for information about ZIEXTENZO that is written for health professionals.

What are the ingredients in ZIEXTENZO?

Active ingredient: pegfilgrastim-bmez

Inactive ingredients: acetic acid, polysorbate 20, sorbitol, and Water for Injection. Sodium hydroxide may be added as necessary to adjust pH.

Manufactured by: Sandoz Inc. Princeton, NJ 08540 US License No. 2003

For more information, visit www.ziextenzo.com or call 1-800-525-8747

This Patient Information has been approved by the U.S. Food and Drug Administration. Revised: 02/2024

Instructions for Use

ZIEXTENZO®

(pegfilgrastim-bmez)

injection

Single-dose prefilled syringe with needle guard

Guide to Parts

Before use

Figure A: Before use. The ZIEXTENZO prefilled syringe with needle guard not activated

Important: The needle is covered by the needle cap before use.

After use

Figure B: After Use. The ZIEXTENZO prefilled syringe with needle guard activated.

Important information:

Read the Patient Information that comes with ZIEXTENZO for important information you need to know about ZIEXTENZO before using these Instructions for Use.

Storing the ZIEXTENZO prefilled syringe

- Store ZIEXTENZO in a refrigerator between 36°F to 46°F (2°C to 8°C).
- Store ZIEXTENZO prefilled syringe in its outer carton to protect it from light or physical damage.
- Take ZIEXTENZO out of the refrigerator at least 15 to 30 minutes before use to allow it to reach room temperature before preparing the injection.
- Avoid freezing. If ZIEXTENZO is accidentally frozen, thaw in the refrigerator before injecting.
- Do not use a ZIEXTENZO prefilled syringe that has been frozen more than 1 time. Use a new ZIEXTENZO prefilled syringe.
- Throw away (dispose of) any ZIEXTENZO that has been left at room temperature 68°F to 95°F (20°C to 35°C) for more than 120 hours. See “14. Disposing of used syringes”.
  Keep ZIEXTENZO and all medicines out of the reach of children.

Important information:

- It is important that you do not try to give the injection unless you or your caregiver have received training from your healthcare provider.
- Make sure that the name ZIEXTENZO appears on the carton and prefilled syringe label.
- Check the carton and prefilled syringe label to make sure the dose strength is 6 mg/0.6 mL.
- You should not inject a dose of ZIEXTENZO to children weighing less than 45 kg from a ZIEXTENZO prefilled syringe. A dose less than 0.6 mL (6 mg) cannot be accurately measured using the ZIEXTENZO prefilled syringe.
- Do not use a ZIEXTENZO prefilled syringe after the expiration date on the label.
- Do not open the outer carton until you are ready to use the ZIEXTENZO prefilled syringe. Do not use the ZIEXTENZO prefilled syringe if the seal of the tray is broken, as it may not be safe for you to use.
- Do not use the ZIEXTENZO prefilled syringe if there is liquid in the plastic tray. Do not use the ZIEXTENZO pre-filled syringe if the needle cap is missing or not securely attached. In all these instances, return the entire product pack to the pharmacy.
- Do not use a prefilled syringe if it has been dropped on a hard surface. The prefilled syringe may be broken even if you cannot see the break. Use a new prefilled syringe.
- Do not shake the ZIEXTENZO prefilled syringe.
- Be careful not to touch the needle guard wings before use. Touching them may cause the needle guard to be activated too early.
- Do not try to activate the needle safety guard before the injection.
- Do not remove the needle cap until just before you give the injection.
- Do not reuse a ZIEXTENZO prefilled syringe. Throw away (dispose of) used syringes right away after use in a sharps disposal container. See “14. Disposing of used syringes”.

Call your healthcare provider if you have any questions.

Prepare the injection.

1. Find a clean, flat, well-lit work surface.
2. Remove the carton from the refrigerator and check the expiration date printed on the carton.
3. Remove the tray containing a ZIEXTENZO prefilled syringe from the carton and place it unopened on your clean work surface for at least 15 to 30 minutes, so that it can reach room temperature.
4. Do not use the prefilled syringe if the carton is damaged.
5. Do not try to warm the prefilled syringe by using a heat source such as hot water or a microwave.
6. Do not leave the prefilled syringe in direct sunlight.
7. Do not shake the prefilled syringe.
4. Wash your hands well with soap and water.

Gather the following supplies for the injection (See Figure C):

- 1 alcohol wipe
- 1 cotton ball or gauze pad
- 1 sharps disposal container
- 1 adhesive bandage

Figure C

5. Open the tray by peeling away the cover. Remove the ZIEXTENZO prefilled syringe from the tray by grabbing the transparent safety guard (See Figure D).
For safety reasons:
3. Do not grab the plunger rod.
4. Do not grab the gray needle cap.

Figure D

Check to be sure that the plastic clear needle guard is located over the barrel of the glass syringe. If the clear needle guard is covering the needle cap, as shown in Figure B above, the needle guard has been activated. Do not try to use this prefilled syringe. Throw away (dispose of) this prefilled syringe. See “14. Disposing of used syringes”. Start over with a new prefilled syringe.

Inspect the prefilled syringe and medicine (See Figure E).

Figure E

6. Make sure that the medicine in the prefilled syringe is clear and colorless to slightly yellowish. You may see small air bubbles in the liquid. This is normal.
Do not use the prefilled syringe if:
3. the medicine looks discolored or cloudy
4. the medicine contains lumps, flakes, or particles
5. it appears used or damaged
6. the needle cap is missing or not securely attached
7. the expiration date printed on the label has passed
In all cases, use a new prefilled syringe and call your healthcare provider.

Select and clean the injection site

Figure F

You can use (See Figure F and Figure G):

- the front of your thighs
- stomach-area (abdomen), except for a 2 inch area right around the navel (belly button)
- upper outer area of the buttocks (only if someone else is giving you the injection
- outer area of upper arm (only if someone else is giving you the injection)

Choose a different site each time you give yourself an injection. Do not inject again in the exact same spot.

Do not inject into areas where the skin is tender, bruised, red, scaly or hard. Avoid areas with scars or stretch marks.

Figure G

7. Clean the injection site with an alcohol wipe. Let the skin dry. Do not touch the cleaned area again before injecting.

Prepare the ZIEXTENZO prefilled syringe for use

Figure H

8. Hold the prefilled syringe by the syringe barrel. Carefully pull the needle cap straight off to remove it from the ZIEXTENZO prefilled syringe (See Figure H).
2. Do not twist or bend the gray needle cap.
3. Do not hold the prefilled syringe by the plunger rod.
Throw away the needle cap in your household trash. Do not put the needle cap back onto the prefilled syringe.
You may see a drop of liquid at the end of the needle. This is normal.

Figure I

9. With your other hand, gently pinch the skin at the injection site to create a firm surface. Insert the needle into the skin at an angle of 45 to 90 degrees, as shown (See Figure I). Push the needle all the way in to ensure that the medicine can be fully injected.

Figure J

10. Hold the ZIEXTENZO prefilled syringe as shown (See Figure J). Slowly press down the plunger head as far as it will go until the plunger head is completely between the needle guard wings.
Important: Keep the skin pinched while injecting.

Figure K

11. Keep the plunger fully pressed down while you carefully pull the needle straight out from the injection site and off your skin (See Figure K).

Figure L

12. Slowly release the plunger and allow the syringe needle guard to automatically cover the exposed needle (See Figure L).
13. There may be a small amount of blood at the injection site. You can press a cotton ball or gauze pad onto the injection site. Do not rub the injection site. Apply an adhesive bandage if needed.

14. Disposing of used syringes

Figure M

Put the used syringes in an FDA-cleared sharps disposal container right away after use (See Figure M). Do not throw away the syringe in the household trash.

- If you do not have an FDA-cleared sharps disposal container, you may use a household container that is:
  - made of a heavy-duty plastic
  - can be closed with a tight-fitting, puncture-resistant lid, without sharps being able to come out
  - upright and stable during use
  - leak-resistant
  - properly labeled to warn of hazardous waste inside the container.
- When your sharps disposal container is almost full, you will need to follow your community guidelines for the right way to dispose of your sharps disposal container. There may be state or local laws about how you should throw away used needles and syringes. For more information about safe sharps disposal, and for specific information about sharps disposal in the state that you live in, go to the FDA’s website at: http://www.fda.gov/safesharpsdisposal.
- Do not reuse the prefilled syringe.
- Do not recycle prefilled syringes or sharps disposal container or throw them into household trash.

Important: Keep the sharps disposal container out of the reach of children.

This Instructions for Use has been approved by the U.S. Food and Drug Administration.

Manufactured by: Sandoz Inc. Princeton, NJ 08540

US License No. 2003.

Revised: Dec 2023

ZIEXTENZO 6 mg/0.6 mL Carton

NDC 61314-866-02

Ziextenzo®6 mg/0.6 mL

(pegfilgrastim-bmez)

Injection

For subcutaneous use only

One Time Use Only

One single-dose prefilled syringe with needle guard

Pegylated Recombinant Methionyl Human Granulocyte Colony-

Stimulating Factor (PEG-r-metHuG-CSF) derived from E coli

No Preservative.

The syringe plunger stopper and needle cap are not made with natural rubber latex.

Rx Only

SANDOZ

A Novartis Division